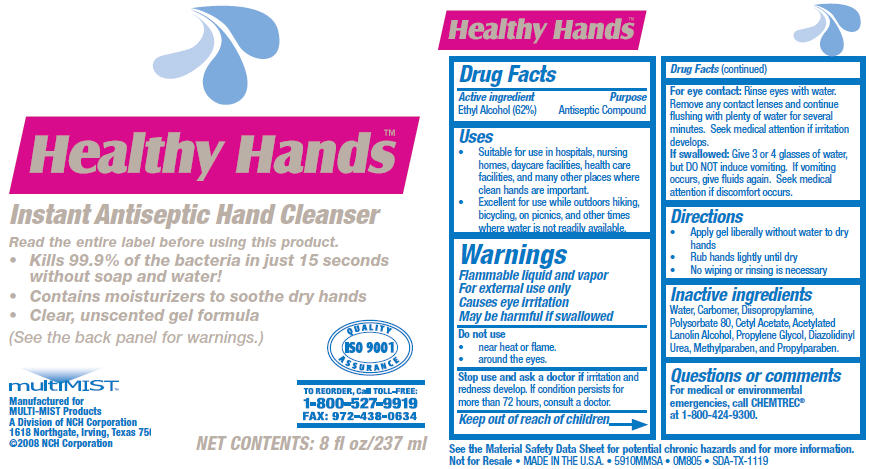 DRUG LABEL: Healthy Hands 
NDC: 55533-522 | Form: SOLUTION
Manufacturer: NCH Corporation
Category: otc | Type: HUMAN OTC DRUG LABEL
Date: 20121211

ACTIVE INGREDIENTS: ALCOHOL 42 mg/25 mL
INACTIVE INGREDIENTS: Water; Diisopropylamine; Polysorbate 80; Propylene Glycol; Diazolidinyl Urea; Methylparaben; Propylparaben

Healthy Hands™
Instant Antiseptic Hand Cleanser

Drug Facts

Active ingredient

Ethyl Alcohol (62%)

Purpose

Antiseptic Compound

Uses

- Suitable for use in hospitals, nursing homes, daycare facilities, health care facilities, and many other places where clean hands are important.
- Excellent for use while outdoors hiking, bicycling, on picnics, and other times where water is not readily available.

Warnings

WHEN USING

Flammable liquid and vapor

For external use only

Causes eye irritation

May be harmful if swallowed

Do not use

- near heat or flame.
- around the eyes.

Stop use and ask a doctor if irritation and redness develop. If condition persists for more than 72 hours, consult a doctor.

Keep out of reach of children

For eye contact

Rinse eyes with water. Remove any contact lenses and continue flushing with plenty of water for several minutes. Seek medical attention if irritation develops.

If swallowed

Give 3 or 4 glasses of water, but DO NOT induce vomiting. If vomiting occurs, give fluids again. Seek medical attention if discomfort occurs.

Directions

- Apply gel liberally without water to dry hands
- Rub hands lightly until dry
- No wiping or rinsing is necessary

Inactive ingredients

Water, Carbomer, Diisopropylamine, Polysorbate 80, Cetyl Acetate, Acetylated Lanolin Alcohol, Propylene Glycol, Diazolidinyl Urea, Methylparaben, and Propylparaben.

Questions or comments

For medical or environmental emergencies, call CHEMTREC® at 1-800-424-9300.

Manufactured for
MULTI-MIST Products
A Division of NCH Corporation
1618 Northgate, Irving, Texas 75

PRINCIPAL DISPLAY PANEL - 237 ml Bottle Label

Healthy Hands™

Instant Antiseptic Hand Cleanser

Read the entire label before using this product.

- Kills 99.9% of the bacteria in just 15 seconds
  without soap and water!
- Contains moisturizers to soothe dry hands
- Clear, unscented gel formula

(See the back panel for warnings.)

multiMIST™

Manufactured for
MULTI-MIST Products
A Division of NCH Corporation
1618 Northgate, Irving, Texas 75
©2008 NCH Corporation

QUALITY
ASSURANCE
ISO 9001

TO REORDER, Call TOLL-FREE:
1-800-527-9919
FAX: 972-438-0634

NET CONTENTS: 8 fl oz/237 ml